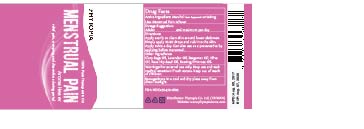 DRUG LABEL: Menstrual Pain Synergy
NDC: 70470-1805 | Form: OIL
Manufacturer: PHYTOPIA CO., LTD.
Category: otc | Type: HUMAN OTC DRUG LABEL
Date: 20171226

ACTIVE INGREDIENTS: MENTHOL 6 mg/50 mL
INACTIVE INGREDIENTS: CLARY SAGE OIL; LAVENDER OIL; BERGAMOT OIL; OLIVE OIL; EVENING PRIMROSE OIL; ROSA RUBIGINOSA SEED OIL

Drug Facts

menthol 0.6mg

Analgesic in the treatment of menstrual pain

Use:

Menstrual Pain reliever

Dosage Suggestion

Adults 4ml maximum per day

Directions

Apply evenly to clean skin around lower abdomen. Simply apply 10~20 drops and rub into the skin. Apply twice a day. Can also use as a preventative by applying before menstrual.

Inactive Ingredients

Clary Sage Oil, Lavender Oil, Bergamot Oil, Olive Oil, Rose Hip Seed Oil, Evening Primrose Oil.

Warnings

For external use only. Stop use and ask doctor if rash occurs. Keep out reach of children.

Other Information

Protect this product from excessive heat

and direct sun.

Warnings

For external use only. Stop use and ask doctor if rash occurs. Keep out reach of children.